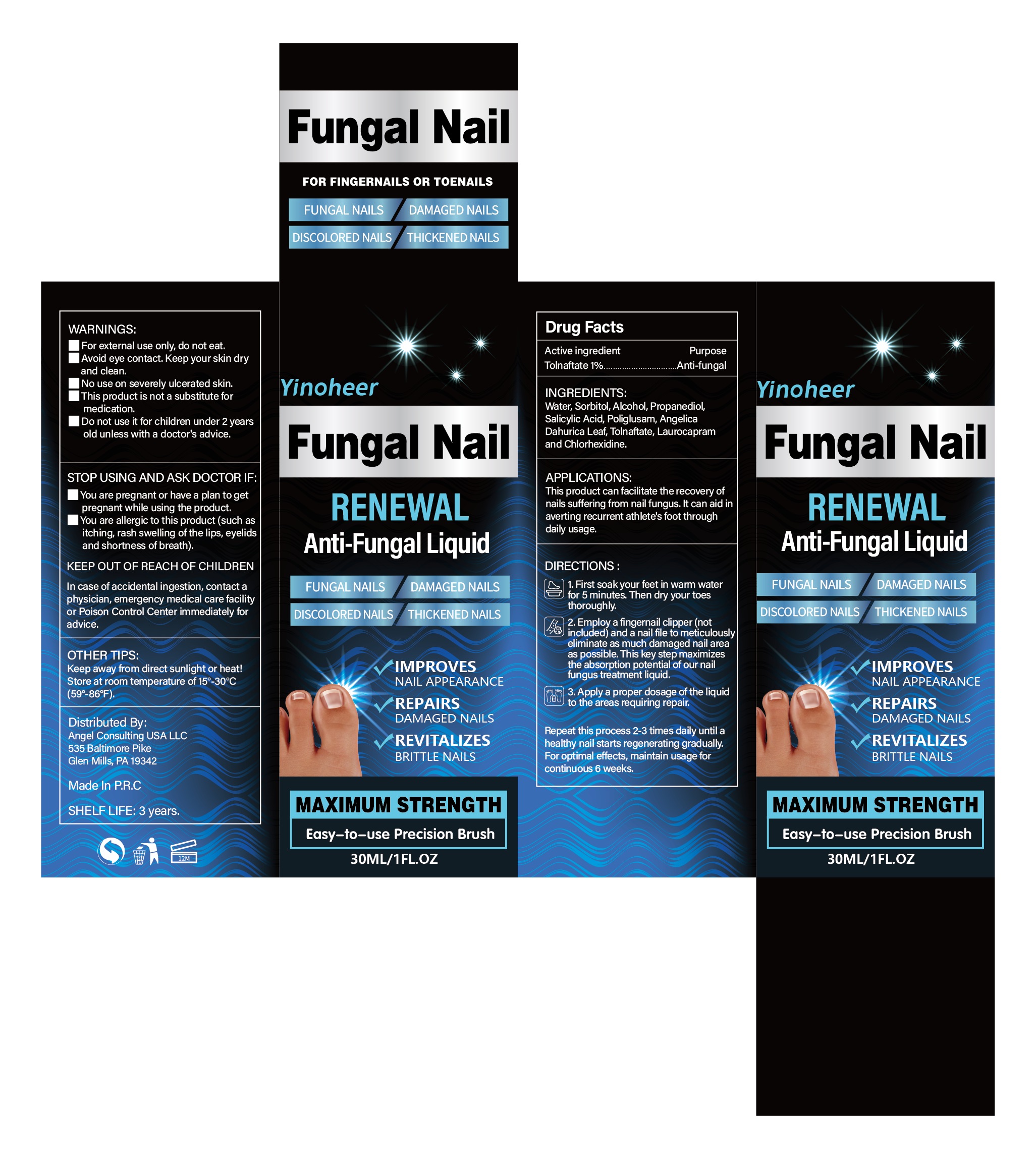 DRUG LABEL: Fungal Nail Liquid
NDC: 84033-006 | Form: LIQUID
Manufacturer: Qingdao Kuajie Online Electronic Technology Co., Ltd
Category: otc | Type: HUMAN OTC DRUG LABEL
Date: 20240409

ACTIVE INGREDIENTS: TOLNAFTATE 1 g/100 mL
INACTIVE INGREDIENTS: ANGELICA DAHURICA LEAF 1.8 g/100 mL; WATER 58.6 mL/100 mL; ALCOHOL 9 mL/100 mL; LAUROCAPRAM 0.3 g/100 mL; POLIGLUSAM 3.4 g/100 mL; PROPANEDIOL 6 g/100 mL; CHLORHEXIDINE 0.2 g/100 mL; SORBITOL 15 g/100 mL; SALICYLIC ACID 4.7 g/100 mL

ACTIVE INGREDIENT

TOLNAFTATE 1%

INACTIVE INGREDIENT

ALCOHOL 9ml

ANGELICA DAHURICA LEAF 1.8g

SORBITOL 15g

SALICYLIC ACID 4.7g

LAUROCAPRAM 0.3g

PROPANEDIOL 6g

CHLORHEXIDINE 0.2g

POLIGLUSAM 3.4g

WATER 58.6ml

PURPOSE

Fungal Nail Renewal

HOW TO USE

1. First soak your feet in warm water for 5 minutes. Then dry your toes thoroughly.

2. Employ a fingernail clipper (not included) and a nail file to meticulously eliminate as much damaged nail area as possible. This key step maximizes the absorption potential of our nail fungus treatment liquid.

3. Apply a proper dosage of the liquid to the areas requiring repair.

WARNINGS

For external use only, do not eat.

Avoid eye contact. Keep your skin dry and clean.

No use on severely ulcerated skin.

This product is not a substitute for medication.

Do not use it for children under 2 years old unless with a doctor's advice.

STOP USE AND ASK A DOCTOR IF

You are pregnant or have a plan to get pregnant while using the product.

You are allergic to this product (such as itching, rash swelling of the lips, eyelids and shortness of breath).

WHEN USING THIS PRODUCT

This product can facilitate the recovery of nails suffering from nail fungus. It can aid in averting recurrent athlete's foot through daily usage.

STORAGE

Keep away from direct sunlight or heat!

Store at room temperature of 15°-30℃ (59°-86℉)

KEEP OUT OF REACH OF CHILDREN

Do not use it for children under 2 years old unless with a doctor's advice.

DOSAGE

Repeat this process 2-3 times daily until a healthy nail starts regenerating gradually.

For optimal effects, maintain usage for continuous 6 weeks.